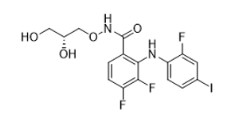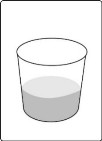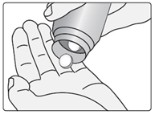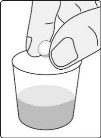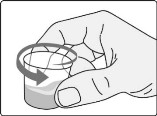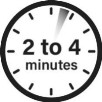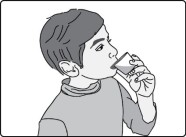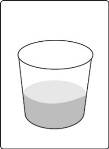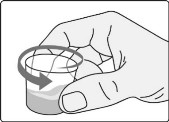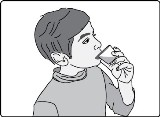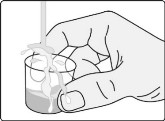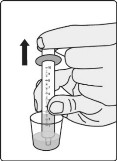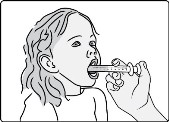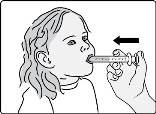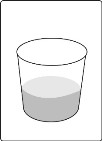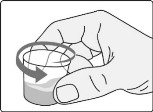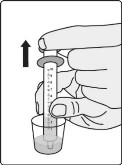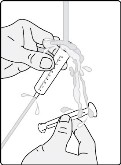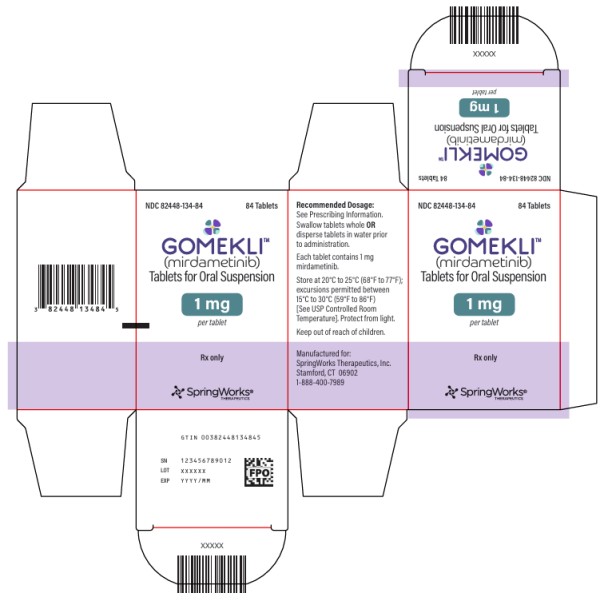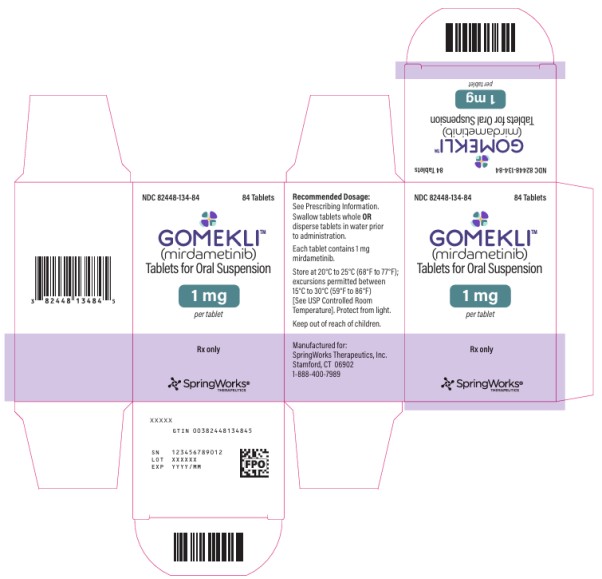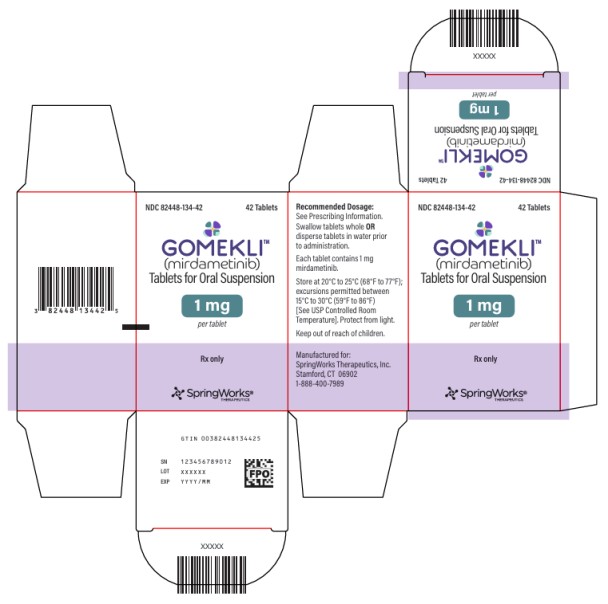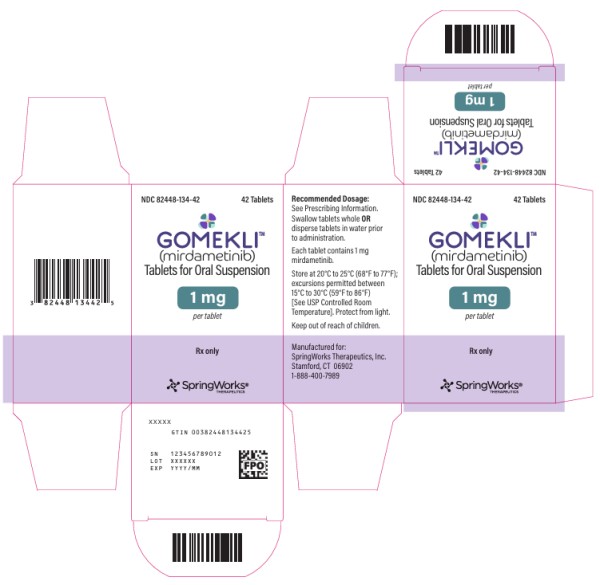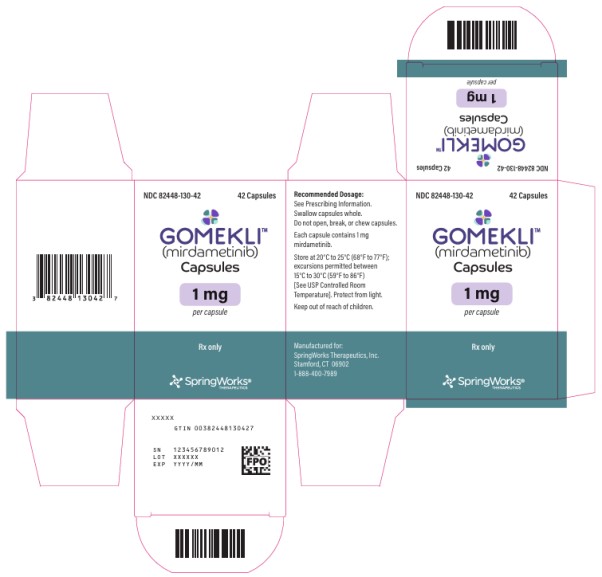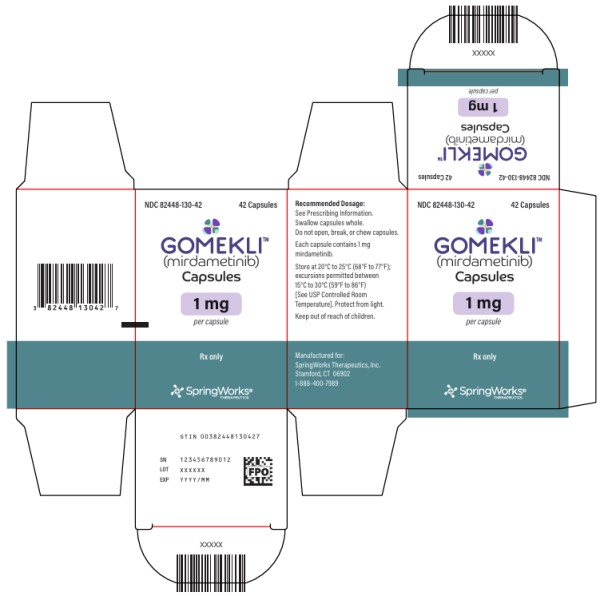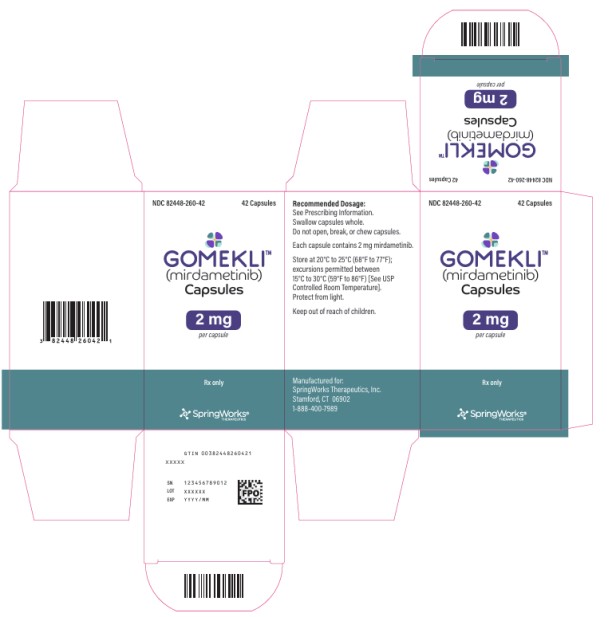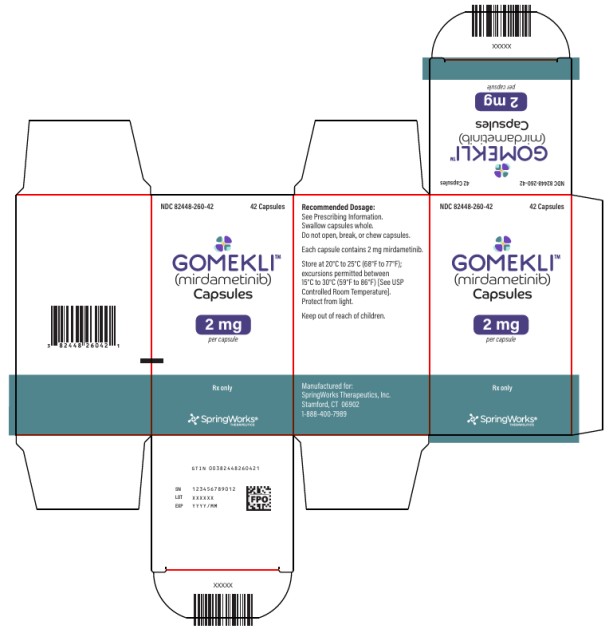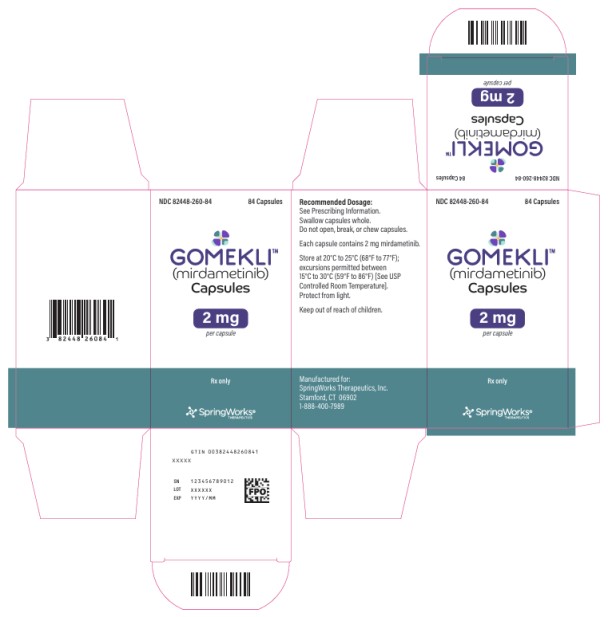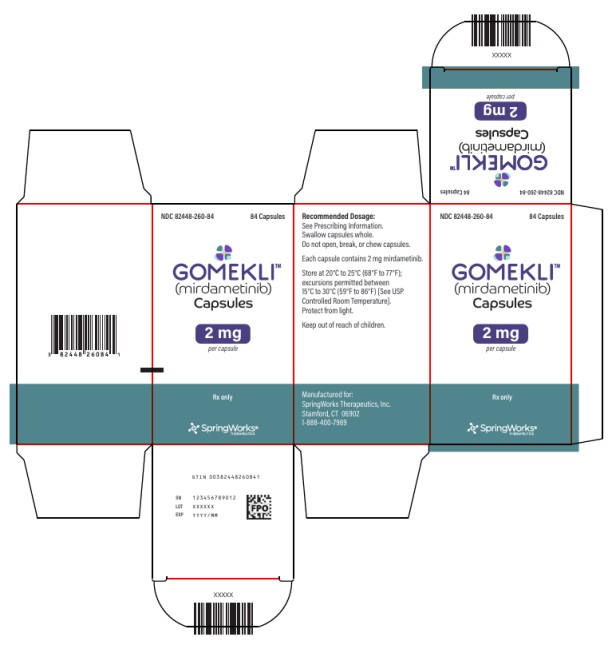 DRUG LABEL: Gomekli
NDC: 82448-130 | Form: CAPSULE
Manufacturer: SpringWorks Therapeutics, Inc.
Category: prescription | Type: HUMAN PRESCRIPTION DRUG LABEL
Date: 20250227

ACTIVE INGREDIENTS: MIRDAMETINIB 1 mg/1 1
INACTIVE INGREDIENTS: CROSCARMELLOSE SODIUM; MAGNESIUM STEARATE; MICROCRYSTALLINE CELLULOSE; FD&C BLUE NO. 1; GELATIN; TITANIUM DIOXIDE; FERRIC OXIDE YELLOW; BUTYL ALCOHOL; DEHYDRATED ALCOHOL; ISOPROPYL ALCOHOL; POTASSIUM HYDROXIDE; PROPYLENE GLYCOL; WATER; SHELLAC; AMMONIA

HIGHLIGHTS OF PRESCRIBING INFORMATION

These highlights do not include all the information needed to use GOMEKLI safely and effectively. See full prescribing information for GOMEKLI.
GOMEKLITM (mirdametinib) capsules, for oral use
GOMEKLITM (mirdametinib) tablets for oral suspension
Initial U.S. Approval: 2025

1 INDICATIONS AND USAGE

GOMEKLI is a kinase inhibitor indicated for the treatment of adult and pediatric patients 2 years of age and older with neurofibromatosis type 1 (NF1) who have symptomatic plexiform neurofibromas (PN) not amenable to complete resection. (1)

2 DOSAGE AND ADMINISTRATION

The recommended dosage of GOMEKLI is 2 mg/m^2 orally twice daily, with or without food, for the first 21 days of each 28-day cycle. Continue treatment with GOMEKLI until disease progression or unacceptable toxicity. (2)

3 DOSAGE FORMS AND STRENGTHS

- Capsules: 1 mg and 2 mg. (3)
- Tablets for Oral Suspension: 1 mg. (3)

4 CONTRAINDICATIONS

None. (4)

5 WARNINGS AND PRECAUTIONS

- Ocular Toxicity: Conduct comprehensive ophthalmic assessments prior to initiating GOMEKLI, at regular intervals during treatment and for new or worsening visual changes or blurred vision. Continue, withhold, reduce the dose, or permanently discontinue GOMEKLI based on severity. (5.1)
- Left Ventricular Dysfunction: Assess ejection fraction by echocardiogram prior to initiating GOMEKLI, every 3 months during the first year, then as clinically indicated thereafter. Withhold, reduce the dose, or permanently discontinue GOMEKLI based on severity. (5.2)
- Dermatologic Adverse Reactions: Initiate supportive care at first signs of dermatologic adverse reactions including rash. Withhold, reduce the dose, or permanently discontinue GOMEKLI based on severity. (5.3)
- Embryo-Fetal Toxicity: Can cause fetal harm. Advise patients of reproductive potential of the potential risk to a fetus and to use effective contraception. (5.4)

6 ADVERSE REACTIONS

Adults:

- The most common adverse reactions (>25%) were rash, diarrhea, nausea, musculoskeletal pain, vomiting, and fatigue. (6.1)
- The most common Grade 3 or 4 laboratory abnormality (>2%) was increased creatine phosphokinase. (6.1)

Pediatric patients:

- The most common adverse reactions (>25%) were rash, diarrhea, musculoskeletal pain, abdominal pain, vomiting, headache, paronychia, left ventricular dysfunction, and nausea. (6.1)
- The most common Grade 3 or 4 laboratory abnormalities (>2%) were decreased neutrophil count and increased creatine phosphokinase. (6.1)

To report SUSPECTED ADVERSE REACTIONS, contact SpringWorks Therapeutics Inc. at 1-888-400-7989 or FDA at 1-800-FDA-1088 or www.fda.gov/medwatch.

8 USE IN SPECIFIC POPULATIONS

- Lactation: Advise not to breastfeed. (8.2)
- Infertility: May impair fertility in females. (8.3)

FULL PRESCRIBING INFORMATION

1 INDICATIONS AND USAGE

GOMEKLI is indicated for the treatment of adult and pediatric patients 2 years of age and older with neurofibromatosis type 1 (NF1) who have symptomatic plexiform neurofibromas (PN) not amenable to complete resection [see Clinical Studies (14)].

2 DOSAGE AND ADMINISTRATION

2.1 Recommended Evaluation and Testing Before Initiating GOMEKLI

Prior to administration of GOMEKLI:

- conduct comprehensive ophthalmic assessment [see Warnings and Precautions (5.1)].
- assess ejection fraction (EF) by echocardiogram [see Warnings and Precautions (5.2)].

2.2 GOMEKLI Dosage Form Overview

GOMEKLI is available in 2 dosage forms: capsules or tablets for oral suspension.

- GOMEKLI capsules: must be swallowed whole, do not open, break or chew capsules.
- GOMEKLI tablets for oral suspension: can be swallowed whole or can be dispersed in drinking water and administered orally as a liquid [see Dosage and Administration (2.4)].

2.3 Recommended Dosage

The recommended dosage of GOMEKLI is 2 mg/m^2 orally twice daily (approximately every 12 hours) with or without food for the first 21 days of each 28-day cycle. The maximum dose is 4 mg twice daily. Continue treatment with GOMEKLI until disease progression or unacceptable toxicity. The recommended dose of GOMEKLI is based on body surface area (BSA) as shown in Table 1.

Table 1: Recommended Dosage for GOMEKLI
Body Surface Area (m^2) * | Recommended Dosage for Capsules or Tablets for Oral Suspension
0.40 to 0.69 | 1 mg twice daily
0.70 to 1.04 | 2 mg twice daily
1.05 to 1.49 | 3 mg twice daily
≥1.50 | 4 mg twice daily

*The recommended dosage for patients with a BSA less than 0.40 m^2 has not been established.

Missed dose: If the patient misses a dose of GOMEKLI, do not take an additional dose. Take the next scheduled dose at the prescribed time.

Vomiting: If vomiting occurs after GOMEKLI administration, do not take an additional dose. Take the next scheduled dose at the prescribed time.

2.4 GOMEKLI Preparation and Administration Instructions

GOMEKLI Capsules

- Swallow GOMEKLI capsules whole with or without food. If more than one capsule is required for a dose, swallow one capsule at a time.
- Do not open, break or chew capsules. Do not administer to patients who are unable to swallow a whole capsule [see GOMEKLI Tablets for Oral Suspension].

GOMEKLI Tablets for Oral Suspension

- GOMEKLI tablets for oral suspension can be swallowed whole with or without food. If more than one tablet is required for a dose, swallow one tablet at a time.
- For patients who are not able to swallow whole tablets, prepare GOMEKLI tablets for oral suspension dispersed in drinking water and administer orally as a liquid [see Instructions for Use].

Preparation and Administration

- Add the prescribed number of tablets to a dosing cup containing approximately 5 mL to 10 mL of drinking water.
- Gently swirl the water and tablets until the tablets are fully dispersed and an oral suspension is obtained. It takes approximately two to four minutes to fully disperse the tablets. Once the tablets are dispersed, the oral suspension will appear white and cloudy.
- Administer the oral suspension immediately after preparation from a dosing cup or oral syringe.
- After administration of the prepared suspension, add approximately 5 mL to 10 mL of drinking water to the dosing cup and gently swirl to resuspend any remaining particles. Administer the suspension to ensure the full dose is taken.
- Discard the oral suspension if not administered within 30 minutes after preparation.

2.5 Dosage Modifications for Adverse Reactions

The recommended dose reductions for adverse reactions are provided in Table 2.

Table 2: Recommended Dose Reductions for GOMEKLI for Adverse Reactions
Body Surface Area (m^2) | Reduced Dose*
 | Morning | Evening
0.40 to 0.69 | 1 mg once daily
0.70 to 1.04 | 2 mg | 1 mg
1.05 to 1.49 | 2 mg | 2 mg
≥1.50 | 3 mg | 3 mg

*Permanently discontinue GOMEKLI in patients unable to tolerate GOMEKLI after one dose reduction.

The recommended dosage modifications for adverse reactions are provided in Table 3.

Table 3: Recommended Dosage Modifications and Management of Adverse Reactions for GOMEKLI
Adverse Reaction | Severity | Dosage Modification
Ocular Toxicity [see Warnings and Precautions (5.1)] | Grade ≤ 2 | - Continue GOMEKLI at current dose level. - Consider ophthalmologic examinations every 2 to 4 weeks until resolution to ≤Grade 1 or baseline.
 | Grade ≥ 3 | - Withhold GOMEKLI until ≤Grade 1 or baseline. - If recovery occurs ≤14 days, resume GOMEKLI at the next lower dose. - If recovery occurs in >14 days, consider permanent discontinuation of GOMEKLI.
 | Symptomatic Retinal Pigment Epithelium Detachment (RPED) | - Withhold GOMEKLI until ≤Grade 1 or baseline. - Resume GOMEKLI at the same dose.
 | Retinal Vein Occlusion (RVO) | - Permanently discontinue GOMEKLI.
Left Ventricular Dysfunction [see Warnings and Precautions (5.2)] | Asymptomatic, absolute decrease in LVEF of 10% or greater from baseline and is less than the lower limit of normal | - Withhold GOMEKLI until ≤Grade 1. - Resume GOMEKLI at reduced dose.
 | Any absolute decrease in LVEF 20% or greater from baseline | - Permanently discontinue GOMEKLI.
Adverse Reaction | Severity | Dosage Modification
Dermatologic Adverse Reactions [see Warnings and Precautions (5.3)] | Intolerable Grade 2 or Grade 3 | - Withhold GOMEKLI until ≤Grade 1. - Resume GOMEKLI at reduced dose.
 | Grade 3 or 4 Dermatitis Acneiform or Non-Acneiform Rash | - Withhold GOMEKLI until ≤Grade 1. - Resume GOMEKLI at reduced dose.
Other Adverse Reactions [see Adverse Reactions (6.1)] | Intolerable Grade 2 or Grade 3 | - Withhold GOMEKLI until ≤Grade 1. - Resume GOMEKLI at reduced dose.
 | Grade 4 | - Consider permanent discontinuation of GOMEKLI.

*Per National Cancer Institute Common Terminology Criteria for Adverse Events version 5.0 (NCI CTCAE v. 5.0).

3 DOSAGE FORMS AND STRENGTHS

Capsules:

- 1 mg: light green body and cap with “MIR 1 mg” printed on the cap in white ink.
- 2 mg: white body and a blue-green cap with “MIR 2 mg” printed on the cap in white ink.

Tablets for Oral Suspension:

- 1 mg: white to off-white, oval, grape flavored tablet, debossed with “S” on one side.

4 CONTRAINDICATIONS

None.

5 WARNINGS AND PRECAUTIONS

5.1 Ocular Toxicity

GOMEKLI can cause ocular toxicity including retinal vein occlusion (RVO), retinal pigment epithelium detachment (RPED), and blurred vision.

In the pooled safety population [see Adverse Reactions (6.1)], ocular toxicity occurred in 25% of patients treated with GOMEKLI: 20% were Grade 1 reactions, 3.8% were Grade 2 reactions, and 0.8% were Grade 3 reactions.

Adult Patients

In the adult pooled safety population [see Adverse Reactions (6.1)], ocular toxicity occurred in 28% of patients treated with GOMEKLI: 21% were Grade 1 reactions, 5% were Grade 2 reactions and 1.3% were Grade 3 reactions. Retinal vein occlusion (RVO) occurred in 2.7% of adult patients, including one Grade 3 reaction which required permanent discontinuation of GOMEKLI. RPED occurred in one adult patient (1.3%). Blurred vision occurred in 9% of adult patients treated with GOMEKLI.

Pediatric Patients

In the pediatric pooled safety population [see Adverse Reactions (6.1)], ocular toxicity occurred in 19% of patients: 17% were Grade 1 and 1.7% were Grade 2.

Conduct comprehensive ophthalmic assessments prior to initiating GOMEKLI, at regular intervals during treatment, and to evaluate any new or worsening visual changes such as blurred vision. Continue, withhold, reduce the dose, or permanently discontinue GOMEKLI as clinically indicated [see Dosage and Administration (2.5)].

5.2 Left Ventricular Dysfunction

GOMEKLI can cause left ventricular dysfunction. Treatment with GOMEKLI has not been studied in patients with a history of clinically significant cardiac disease or LVEF <55% prior to initiation of treatment.

In the ReNeu study, in adult and pediatric patients [see Adverse Reactions (6.1)], decreased LVEF of 10 to <20% occurred in 20%, and decreased LVEF of ≥20% occurred in 0.9% of patients treated with GOMEKLI. All patients with decreased LVEF were identified during routine echocardiography. Decreased LVEF resolved in 75% of these patients.

Adult Patients

In adult patients in the ReNeu study [see Adverse Reactions (6.1)], decreased LVEF of 10 to <20% occurred in 16% of adult patients treated with GOMEKLI. Of the adult patients with decreased LVEF, five patients (9%) required dose interruption, one patient (1.7%) required a dose reduction and one patient required permanent discontinuation of GOMEKLI. The median time to first onset of decreased LVEF in adult patients was 70 days.

Pediatric Patients

In pediatric patients in the ReNeu study [see Adverse Reactions (6.1)], decreased LVEF of 10 to <20% occurred in 25%, and decreased LVEF of ≥20% occurred in 1.8% of patients treated with GOMEKLI. Of the pediatric patients with decreased LVEF, one patient (1.8%) required dose interruption of GOMEKLI. The median time to first onset of decreased LVEF in pediatric patients was 132 days.

Before initiating GOMEKLI, assess ejection fraction (EF) by echocardiogram. Monitor EF every 3 months during the first year and then as clinically indicated. Withhold, reduce the dose, or permanently discontinue GOMEKLI based on the severity of adverse reaction [see Dosage and Administration (2.5)].

5.3 Dermatologic Adverse Reactions

GOMEKLI can cause dermatologic adverse reactions including rash.

In the pooled safety population [see Adverse Reactions (6.1)], rash occurred in 84% of patients treated with GOMEKLI: 31% were Grade 2, and 6% were Grade 3. The most frequent rashes (≥2%) included dermatitis acneiform (65%), rash (11%), eczema (8%), maculo-papular rash (4.5%) and pustular rash (3.8%).

Adult Patients

In the pooled adult safety population [see Adverse Reactions (6.1)], rash occurred in 92% of patients treated with GOMEKLI: 37% were Grade 2 and 8% were Grade 3 reactions. Rash requiring permanent discontinuation of GOMEKLI occurred in 11% of adult patients.

Pediatric Patients

In the pooled pediatric safety population [see Adverse Reactions (6.1)], rash occurred in 72% of patients treated with GOMEKLI: 22% were Grade 2 and 3.4% were Grade 3 reactions.

Rash resulting in permanent discontinuation of GOMEKLI occurred in 3.4% of pediatric patients.

Dermatitis acneiform occurred with a higher frequency in patients aged 12 to 17 years (77%) than those aged 2 to 11 years (16%), while non-acneiform rashes occurred with a higher frequency in patients aged 2 to 11 years (53%) than those aged 12 to 17 years (15%).

Initiate supportive care at first signs of dermatologic adverse reactions. Withhold, reduce the dose, or permanently discontinue GOMEKLI based on severity of adverse reaction [see Dosage and Administration (2.5)].

5.4 Embryo-Fetal Toxicity

Based on findings from clinical trials, animal studies and its mechanism of action, GOMEKLI can cause fetal harm when administered to a pregnant woman. In ReNeu, a pregnancy reported 31 days after the last dose of GOMEKLI resulted in a first trimester spontaneous abortion.

In embryo-fetal development studies, oral administration of mirdametinib to pregnant rats and rabbits during the period of organogenesis resulted in embryo-fetal mortality, structural abnormalities and alterations to growth at doses approximately equivalent to the human clinical dose of 2 mg/m^2 twice daily based on body surface area (BSA).

Verify the pregnancy status of females of reproductive potential prior to the initiation of GOMEKLI. Advise pregnant women and females of reproductive potential of the potential risk to a fetus. Advise females of reproductive potential to use effective contraception during treatment with GOMEKLI and for 6 weeks after the last dose. Advise males with female partners of reproductive potential to use effective contraception during treatment with GOMEKLI and for 3 months after the last dose [see Use in Specific Populations (8.1, 8.3)].

6 ADVERSE REACTIONS

The following serious adverse reactions are described elsewhere in the labeling:

- Ocular Toxicity [see Warnings and Precautions (5.1)]
- Left Ventricular Dysfunction [see Warnings and Precautions (5.2)]
- Dermatologic Adverse Reactions [see Warnings and Precautions (5.3)]
- Embryo-Fetal Toxicity [see Warnings and Precautions (5.4)]

6.1 Clinical Trials Experience

Because clinical trials are conducted under widely varying conditions, adverse reaction rates observed in the clinical trials of a drug cannot be directly compared to rates in the clinical trials of another drug and may not reflect the rates observed in practice.

The pooled safety population described in the WARNINGS AND PRECAUTIONS reflects exposure to GOMEKLI in 133 patients (75 adults and 58 pediatric patients) in the ReNeu study [see Clinical Studies (14)] (n=114) and Study NF-106 (n=19) [NCT-02096471].

Patients received GOMEKLI 2 mg/m^2 orally twice daily for the first 21 days of each 28-day cycle until disease progression or unacceptable toxicity. Among 133 patients who received GOMEKLI, 62% were exposed for one year or longer, 38% were exposed for 2 years or longer, and 12% were exposed for 3 years or longer.

Neurofibromatosis Type 1-Associated Plexiform Neurofibromas

The safety of GOMEKLI was evaluated in the ReNeu study [see Clinical Studies (14)]. Eligible patients were 2 years of age and older with neurofibromatosis type 1 (NF1) who had symptomatic plexiform neurofibromas (PN). Patients were excluded for abnormal left ventricular ejection fraction (LVEF), uncontrolled hypertension, alanine transaminase (ALT) value of >2 × upper limit of normal (ULN), any current or history of retinal vein occlusion (RVO) or retinal pigment epithelium detachment (RPED), intraocular pressure >21 mmHg (or upper limit of normal adjusted by age), and history of glaucoma. Patients received GOMEKLI 2 mg/m2 orally twice daily for the first 21 days of each 28-day cycle until disease progression or unacceptable toxicity.

Adult Patients

The median age of adult patients (age ≥18) who received GOMEKLI was 35 years (range: 18-69); 64% were female; 85% were White, 9% were Black or African American, 3.4% were Asian, 3.4% were other races or race not reported; and 1.7% were Hispanic or Latino. For adult patients treated with GOMEKLI, the median duration of treatment was 22 months (range: 0.4 to 46 months).

Serious adverse reactions occurred in 17% of adult patients who received GOMEKLI. Serious adverse reactions occurring in ≥1% of patients were COVID-19 (3.4%), nephrolithiasis (3.4%), and in 1 patient each: acute kidney injury, abdominal pain, ischemic colitis, urinary tract infection, retinal vein occlusion, scoliosis, squamous cell carcinoma of skin, cerebrovascular accident and chronic obstructive pulmonary disease. One fatal adverse reaction occurred in an adult patient (1.7%) who received GOMEKLI, due to COVID-19.

Permanent discontinuation of GOMEKLI due to an adverse reaction occurred in 22% of adult patients. Adverse reactions which resulted in permanent discontinuation of GOMEKLI in ≥1% of adult patients were rash, diarrhea, nausea, abdominal pain, alopecia, dry skin, left ventricular dysfunction, cough, wheezing, COVID-19, peripheral swelling, RVO, dizziness, and vomiting.

Dosage interruptions of GOMEKLI due to an adverse reaction occurred in 31% of adult patients. Adverse reactions which required dosage interruption in ≥5% of patients included left ventricular dysfunction and COVID-19.

Dose reductions of GOMEKLI due to an adverse reaction occurred in 17% of adult patients. Adverse reactions which required dose reductions in ≥5% of patients included rash.

The most common adverse reactions (>25%) were rash, diarrhea, nausea, musculoskeletal pain, vomiting, and fatigue. The most common Grade 3 or 4 laboratory abnormality (>2%) was increased creatine phosphokinase.

Pediatric Patients

The median age of pediatric patients (age ≤17 years) who received GOMEKLI was 10 years (range: 2 to 17); 54% were female; 66% were White, 20% were Black or African American, 9% were other races or race not reported, 3.6% were Asian, 1.8% were American Indian or Alaska Native; and 14% were Hispanic or Latino. For pediatric patients treated with GOMEKLI, the median duration of treatment was 22 months (range: 1.6 to 40 months).

Serious adverse reactions occurred in 14% of pediatric patients who received GOMEKLI. Serious adverse reactions in ≥1% of patients included viral gastrointestinal infections (3.6%) and in 1 patient each: diplopia, musculoskeletal pain, seizure, fall, femoral neck fracture, dehydration and hypertension.

Permanent discontinuation of GOMEKLI due to an adverse reaction occurred in 9% of pediatric patients. Adverse reactions that required permanent discontinuation of GOMEKLI in ≥1% of patients were urticaria, rash, abdominal pain, constipation, and diarrhea.

Dosage interruptions of GOMEKLI due to an adverse reaction occurred in 30% of pediatric patients. Adverse reactions which required dosage interruption in ≥5% of patients included COVID-19.

Dose reductions of GOMEKLI due to an adverse reaction occurred in 13% of pediatric patients. Adverse reactions which required dosage reduction in ≥3% of pediatric patients were rash and decreased neutrophil count.

The most common adverse reactions (>25%) were rash, diarrhea, musculoskeletal pain, abdominal pain, vomiting, headache, paronychia, left ventricular dysfunction, and nausea. The most common Grade 3 or 4 laboratory abnormalities (>2%) were decreased neutrophil count and increased creatine phosphokinase.

Table 4: Adverse Reactions (≥20%) in Adult and Pediatric Patients with NF1- Associated PN Who Received GOMEKLI in ReNeu
 | Adult N=58 |  | Pediatric N=56 |  | Total N=114
 | All Grades (%) | Grade 3 or 4 a (%) | All Grades (%) | Grade 3 or 4 a (%) | All Grades (%) | Grade 3 or 4 a (%)
Skin and Subcutaneous Tissue Disorders
Rashb | 90 | 10 | 73 | 3.6 | 82 | 7
Gastrointestinal Disorders
Diarrheac | 59 | 0 | 55 | 5 | 57 | 2.6
Nausea | 52 | 0 | 27 | 0 | 40 | 0
Vomiting | 38 | 0 | 39 | 0 | 39 | 0
Abdominal Paind | 24 | 3.4 | 39 | 3.6 | 32 | 3.5
Stomatitise | 5 | 0 | 20 | 0 | 12 | 0
Musculoskeletal and Connective Tissue Disorders
Musculoskeletal Painf | 41 | 5 | 41 | 1.8 | 41 | 3.5
General Disorders and Administration Site Conditions
Fatigue | 29 | 1.7 | 13 | 0 | 21 | 0.9
Pyrexia | 7 | 0 | 20 | 0 | 13 | 0
Infections and Infestations
COVID-19g | 22 | 5 | 25 | 0 | 24 | 2.6
Paronychia | 1.7 | 0 | 32 | 0 | 17 | 0
Upper Respiratory Tract Infection | 0 | 0 | 23 | 0 | 11 | 0
Nervous System Disorders
Headacheh | 14 | 1.7 | 34 | 1.8 | 24 | 1.8
Peripheral Neuropathyi | 21 | 0 | 3.6 | 0 | 12 | 0
Cardiac Disorders
Left Ventricular Dysfunction | 16 | 0 | 27 | 1.8 | 21 | 0.9
Respiratory, Thoracic and Mediastinal Disorders
Coughj | 9 | 0 | 21 | 0 | 15 | 0

a All reactions were Grade 3 except one fatal case of COVID-19 in an adult.

b Rash includes dermatitis acneiform, eczema, maculo-papular rash, pustular rash, dermatitis, erythematous rash, palmar-plantar erythrodysaesthesia syndrome, exfoliative rash, skin exfoliation, pruritic rash, papule, papular rash and macular rash.

c Diarrhea includes frequent bowel movements.

d Abdominal pain includes upper abdominal pain, gastrointestinal pain and abdominal discomfort.

e Stomatitis includes mouth ulceration, aphthous ulcer.

f Musculoskeletal pain includes non-cardiac chest pain, back pain, pain in extremity, neck pain, musculoskeletal chest pain, myalgia, arthralgia, and bone pain.

g Includes one fatal case in an adult.

h Headache includes migraine.

i Peripheral neuropathy includes paresthesia, hypoesthesia, neuralgia, peripheral sensory neuropathy.

j Cough includes upper-airway cough syndrome.

Clinically relevant adverse reactions that occurred in <20% of patients include:

- Skin and Subcutaneous Tissue Disorders: alopecia, hair color changes
- Gastrointestinal Disorders: constipation
- Eye Disorders: retinal vein occlusion (RVO), retinal pigment epithelium detachment (RPED) and blurred vision

Table 5 summarizes the laboratory abnormalities in ReNeu.

Table 5: Select Laboratory Abnormalities (≥15%) that Worsened from Baseline in Adult and Pediatric Patients with NF1-Associated PN Who Received GOMEKLI in ReNeu
 | Adulta |  | Pediatricb |  | Totalc
Laboratory Abnormalityd,e | All Grades (%) | Grade 3 or 4 d (%) | All Grades (%) | Grade 3 or 4 d (%) | All Grades (%) | Grade 3 or 4 d (%)
Chemistry
Increased Creatine Phosphokinase | 55 | 3.6 | 59 | 5 | 57 | 4.5
Increased Triglycerides | 29 | 0 | 45 | 0 | 37 | 0
Decreased Glucose | 5 | 0 | 36 | 1.8 | 21 | 0.9
Decreased Calciumf | 23 | 0 | 20 | 0 | 21 | 0
Increased Creatinine | 13 | 0 | 30 | 0 | 21 | 0
Increased Cholesterol | 23 | 0 | 16 | 0 | 20 | 0
Increased Alkaline Phosphatase | 13 | 0 | 29 | 0 | 21 | 0
Decreased Bicarbonate | 11 | 0 | 21 | 0 | 16 | 0
Increased Alanine Aminotransferase (ALT) | 9 | 0 | 21 | 0 | 15 | 0
Increased Aspartate Aminotransferase (AST) | 18 | 0 | 9 | 0 | 13 | 0
Hematology
Decreased Hemoglobin | 21 | 0 | 29 | 0 | 25 | 0
Decreased Leukocytes | 7 | 0 | 40 | 0 | 23 | 0
Decreased Neutrophils | 7 | 0 | 31 | 11 | 19 | 5
Increased Lymphocytes | 7 | 0 | 27 | 0 | 17 | 0
Decreased Lymphocytes | 16 | 0 | 1.8 | 0 | 9 | 0

a The denominator used to calculate the rate was 56 based on the number of patients with a baseline value and at least one post-treatment value.

b The denominator used to calculate the rate varied from 55 to 56 based on the number of patients with a

baseline value and at least one post-treatment value.

c The denominator used to calculate the rate varied from 111 to 112 based on the number of patients with a baseline value and at least one post-treatment value.

d Graded per NCI-CTCAE version 5.0.

e No Grade 5 laboratory abnormalities were reported in the ReNeu study.

f Calcium corrected for albumin (mmol/L).

8 USE IN SPECIFIC POPULATIONS

8.1 Pregnancy

Risk Summary

Based on findings from clinical trials, animal studies, and its mechanism of action [see Clinical Pharmacology (12.1)], GOMEKLI can cause fetal harm or loss of pregnancy when administered to a pregnant woman. In embryo-fetal development studies, oral administration of mirdametinib to pregnant rats and rabbits during the period of organogenesis caused embryo-fetal mortality, structural abnormalities and alterations to growth at doses that were approximately equivalent to the human clinical dose of 2 mg/m^2 twice daily based on BSA (see Data). Advise pregnant women of the potential risk to a fetus.

In the U.S. general population, the estimated background risk of major birth defects and miscarriage in clinically recognized pregnancies is 2% to 4% and 15% to 20%, respectively.

Data

Human Data

In ReNeu, a pregnancy reported 31 days after the last dose of GOMEKLI resulted in a first trimester spontaneous abortion.

Animal Data

In an embryo-fetal developmental toxicity study, mirdametinib was administered orally to pregnant rats during the period of organogenesis (gestation days 6 to 17) at doses of 0.3, 0.6, 3 or 5 mg/kg/day. Mirdametinib caused post-implantation loss and decreased fetal body weights at doses ≥3 mg/kg/day (≥5 times the human clinical dose of 2 mg/m^2 twice daily based on BSA). Multiple malformations, including shortening of limbs and absence or shortening of digits, were observed in one fetus and another with hyperflexion variation at the dose of 3 mg/kg/day.

In an embryo-fetal developmental toxicity study, mirdametinib was administered orally to pregnant rabbits during the period of organogenesis (gestation day 7 to 19) at doses of 0.3, 1, 3, or 6 mg/kg/day. Maternal toxicity (decreased body weight and moribund condition) was observed at doses ≥1 mg/kg/day (≥3 times the human clinical dose of 2 mg/m^2 twice daily based on BSA). Two animals had spontaneous abortions at the 1 mg/kg dose on Days 20 and 23. Mirdametinib caused post-implantation loss at doses ≥0.3 mg/kg/day (approximately equivalent to the human clinical dose of 2 mg/m^2 twice daily based on BSA).

8.2 Lactation

Risk Summary

There are no data on the presence of mirdametinib or its metabolites in human milk or their effects on a breastfed child or on milk production. Because of the potential for adverse reactions in breastfed children, advise women not to breastfeed during treatment with GOMEKLI and for 1 week after the last dose.

8.3 Females and Males of Reproductive Potential

GOMEKLI can cause fetal harm when administered to a pregnant woman [see Use in Specific Populations (8.1)].

Pregnancy Testing

Verify the pregnancy status of females of reproductive potential prior to initiating GOMEKLI.

Contraception

Females

Advise females of reproductive potential to use effective contraception during treatment with GOMEKLI and for 6 weeks after the last dose.

Males

Advise male patients with female partners of reproductive potential to use effective contraception during treatment with GOMEKLI and for 3 months after the last dose.

Infertility

Based on findings in animals, GOMEKLI may impair fertility in females of reproductive potential. The reversibility of the effects on female fertility in animals is unknown [see Nonclinical Toxicology (13.1)].

8.4 Pediatric Use

The safety and effectiveness of GOMEKLI have been established in pediatric patients 2 years of age and older with NF1-PN based on the results of the ReNeu study, a single-arm trial conducted in 58 pediatric patients age ≥2 years [see Clinical Studies (14.1)]. The ReNeu study demonstrated improvement in overall response rate per REiNS criteria and duration of response.

The safety and effectiveness of GOMEKLI have not been established in pediatric patients younger than 2 years old.

Animal Toxicity Data

In a 3-month repeat-dose toxicology study in rats, oral administration of mirdametinib at doses ≥0.3 mg/kg/day (≥2 times the human exposure at the clinical dose of 2 mg/m2 twice daily based on AUC) resulted in dysplasia in femoral epiphyseal growth plate, metaphyseal hypocellularity of the bone marrow of long bones, and metaphyseal thickening of bone trabeculae of long bones; male rats were more sensitive to these effects.

8.5 Geriatric Use

Of the 133 patients with neurofibromatosis type 1 (NF1) with symptomatic plexiform neurofibromas (PN) who received GOMEKLI 2 mg/m^2 orally twice daily for the first 21 days of each 28-day cycle until disease progression or unacceptable toxicity, 2 (1.5%) were 65 years of age and older and none were 75 years of age and older. Clinical studies of GOMEKLI did not include sufficient numbers of patients 65 years of age and older to determine whether they respond differently than younger adult patients.

8.6 Renal Impairment

No dosage adjustment is required in patients with mild (creatinine clearance: 60-89 mL/min) or moderate (creatinine clearance: 30-59 mL/min) renal impairment. GOMEKLI has not been studied in patients with severe (creatinine clearance <30 mL/min) renal impairment [see Clinical Pharmacology (12.3)].

8.7 Hepatic Impairment

No dosage adjustment is required in patients with mild hepatic impairment (total bilirubin ≤ upper limit of normal (ULN) and aspartate aminotransferase (AST) > ULN, or total bilirubin in 1-1.5 x ULN).

The pharmacokinetics of mirdametinib in patients with moderate (bilirubin >1.5 to 3 x ULN and any AST) or severe (bilirubin >3 x ULN and any AST) hepatic impairment has not been evaluated [see Clinical Pharmacology (12.3)].

11 DESCRIPTION

GOMEKLI capsules and tablets for oral suspension contain mirdametinib, a kinase inhibitor. Mirdametinib is chemically known as (R)-N-(2,3-dihydroxypropoxy)-3,4-difluoro-2-((2- fluoro-4-iodophenyl)amino) benzamide. The molecular formula is C16H14 F3IN2O4 and the molecular weight is 482.20 g/mol. The structural formula for mirdametinib is:

Mirdametinib is a white to tan or pink solid with an aqueous solubility of 0.25 mg/mL and a pH of 7.2 in water at 25°C. The molecule has a pKa of 7.96.

GOMEKLI capsules and tablets for oral suspension are immediate release (IR) dosage forms intended for oral administration.

GOMEKLI (mirdametinib) 1 mg and 2 mg capsules contain 1 mg and 2 mg mirdametinib, respectively, in gelatin capsule and the following inactive ingredients: croscarmellose sodium, magnesium stearate, and microcrystalline cellulose. The gelatin capsule shell contains FD&C blue #1, gelatin, titanium dioxide, and yellow iron oxide. The capsule is imprinted with white ink that contains butyl alcohol, dehydrated alcohol, isopropyl alcohol, potassium hydroxide, propylene glycol, purified water, shellac, strong ammonia solution, and titanium dioxide.

GOMEKLI (mirdametinib) 1 mg tablets for oral suspension contain 1 mg mirdametinib and the following inactive ingredients: croscarmellose sodium, magnesium stearate, microcrystalline cellulose, grape flavor, and sucralose. The grape flavor includes corn syrup solids, modified corn starch, and triacetin.

12 CLINICAL PHARMACOLOGY

12.1 Mechanism of Action

Mirdametinib is an inhibitor of mitogen-activated protein kinase kinases 1 and 2 (MEK1/2). MEK1/2 proteins are upstream regulators of the extracellular signal-related kinase (ERK) pathway. In vitro, mirdametinib inhibited kinase activity of MEK1 and MEK2 and downstream phosphorylation of ERK.

In a mouse model of NF1, oral dosing of mirdametinib inhibited ERK phosphorylation and reduced neurofibroma tumor volume and proliferation.

12.2 Pharmacodynamics

Mirdametinib exposure-response relationships and the time course of pharmacodynamic response are not fully characterized.

Cardiac Electrophysiology

At approximately six times the steady-state exposure associated with the recommended dose of 2 mg/m^2, clinically significant QTc interval prolongation was not observed.

12.3 Pharmacokinetics

GOMEKLI pharmacokinetic parameters are summarized in Table 6.

Table 6: Pharmacokinetic Parameters and Characteristics of Mirdametinib
General Information
Steady-state [mean (%CV)] | Cmax | - Adult patients (≥18 years): 188 (52%) ng/mL - Pediatric patients (2 to17 years): 191 (62%) ng/mL
 | AUC | - Adult patients (≥18 years): 431 (43%) ng·h/mL - Pediatric patients (2 to 17 years): 459 (46%) ng·h/mL
Time to steady-state |  | Approximately 6 days
Accumulation ratio (AUC) [mean] |  | 1.1 to 1.9
Absorption
Tmax [median (min, max)] |  | - Tablet: 0.8 (0.4-3) hours post-dose - Capsule: 1.1 (0-4) hours post-dose
Absolute bioavailability |  | No data are available in humans
Food effect [GMR% (90% CI)] (high-fat, high-calorie meal) | Cmax | 57% (54%, 61%)
 | AUCinf | 93% (90%, 96%)
Distribution
Human plasma protein binding |  | Greater than 99%
Apparent volume of distribution [mean (%CV)] |  | 255 L (13%)
Elimination
Apparent systemic clearance [mean (%CV)] |  | 6.3 L/h (13%)
Terminal elimination half-life [mean (%CV)] |  | 28 h (12%)
Metabolism
Primary pathway |  | Metabolism involves glucuronidation and oxidation via UGT (primarily UGT1A6 and UGT2B7) and CES enzymes.
Excretion
Radioactivity |  | - In urine: 68% - In feces: 27%
Unchanged mirdametinib |  | - In urine and feces: 9% - In urine: 0.7%

Abbreviations: AUC: area under the plasma concentration-time curve; AUCinf: AUC from dosing extrapolated to infinity; CI: confidence interval; CES: carboxyl esterase enzyme; Cmax: maximum plasma concentration; CV: coefficient of variation; GMR: geometric least squares mean ratio; UGT: uridine diphosphate (UDP)- glycosyltransferase

Specific Populations

Effects of Age, Sex, and Race

No clinically significant differences in mirdametinib pharmacokinetics were observed based on age (2 to 86 years), sex, and race (11% African American or Black, 12% Asian, 72% White). The effects of moderate or severe hepatic impairment, severe renal impairment, or end-stage renal disease (ESRD) on mirdametinib pharmacokinetics are unknown.

Drug Interaction Studies

No clinical DDI studies have been conducted. The effect of concomitant strong CYP3A4 inducers (that also co-induce UGTs, P-gp, and CES enzymes) on mirdametinib PK is currently unknown.

In Vitro Studies

CYP Enzymes: Mirdametinib does not inhibit CYP1A2, CYP2B6, CYP2C8, CYP2C9, CYP2C19, CYP2D6, or CYP3A4.

Mirdametinib does not induce CYP1A2, CYP2B6, CYP2C8, CYP2C9, CYP2C19, or CYP3A4.

Transporter Systems: Mirdametinib does not inhibit BCRP, P-gp, OATP1B1, OATP1B3, OCT2, OAT1, OAT3, MATE1, or MATE2K transporters.

Mirdametinib is a substrate of BCRP and P-gp transporters.

13 NONCLINICAL TOXICOLOGY

13.1 Carcinogenesis, Mutagenesis, Impairment of Fertility

Mirdametinib was not carcinogenic in a 6-month study in transgenic rasH2 mice that received oral doses up to 5 mg/kg/day (approximately 15 times the human exposure at the clinical dose of 2 mg/m^2 twice daily based on AUC).

Mirdametinib was not mutagenic in an in vitro bacterial reverse mutation (Ames) assay. Mirdametinib was not clastogenic in an in vitro human lymphocyte chromosomal aberration assay or in an in vivo rat bone marrow chromosomal aberration assay. Mirdametinib was positive in the in vivo micronucleus assay in rats.

In a dedicated fertility study, male rats were treated with mirdametinib for 28 days before mating with untreated females to Gestational Day 1. Female rats were treated with mirdametinib for 14 days before mating with untreated males to Gestational Day 7. No effects on mating performance or fertility in males or females were observed at doses up to 1 mg/kg/day (approximately 2 times the human clinical dose of 2 mg/m^2 twice daily based on BSA). In a 3-month repeat-dose toxicology study in rats, mirdametinib caused decreased ovarian organ weight and increased follicular cysts associated with decreases in the number of corpora lutea at doses ≥0.3 mg/kg/day (approximately 2 times the human exposure at the clinical dose of 2 mg/m^2 twice daily based on AUC). Findings in male rats included hypoplasia of the spermatogenic epithelium in the testis, decreased content in the epididymis, and inflammation of the prostate at 1 mg/kg (approximately 8-times the human exposure at the clinical dose of 2 mg/m^2 based on AUC). The reversibility of effects on ovary and male reproductive organs was not assessed.

14 CLINICAL STUDIES

14.1 Neurofibromatosis Type 1 Associated Plexiform Neurofibromas

The efficacy of GOMEKLI was evaluated in the ReNeu study (NCT03962543), a multicenter, single-arm study in 114 patients ≥2 years of age with symptomatic, inoperable neurofibromatosis type 1 (NF1) associated plexiform neurofibromas (PN) causing significant morbidity. An inoperable PN was defined as a PN that cannot be completely surgically removed without risk for substantial morbidity due to: encasement of or close proximity to vital structures, invasiveness, or high vascularity of the PN. Patients received GOMEKLI 2 mg/m^2 orally twice daily for the first 21 days of each 28-day cycle until disease progression or unacceptable toxicity.

The major efficacy outcome measure was confirmed overall response rate (ORR), defined as the percentage of patients with complete response (disappearance of the target PN) or partial response (≥20% reduction in PN volume). Responses were assessed by blinded independent central review (BICR) using volumetric magnetic resonance imaging (MRI) analysis per Response Evaluation in Neurofibromatosis and Schwannomatosis (REiNS) criteria modified to be confirmed at a subsequent tumor assessment within 2 to 6 months during the 24-cycle treatment phase. A secondary efficacy outcome measure was duration of response for patients who achieved a confirmed response.

Adults

A total of 58 adult patients received GOMEKLI. The median age was 35 years (range 18 to 69 years); 64% were female, 85% were White, 9% were Black or African American, 3.4% were Asian, 3.4% were other races; and 1.7% were Hispanic or Latino. Approximately half of the patients (53%) had a progressing PN at study entry, 7% had prior treatment with a MEK inhibitor and 69% had prior surgery. Morbidities reported in >25% of patients were pain (90%), disfigurement or major deformity (52%), and motor dysfunction (40%).

Pediatric Patients

A total of 56 pediatric patients received GOMEKLI. The median age was 10 years (range: 2 to 17); 54% were female; 66% were White, 20% were Black or African American, 9% were other races, 3.6% were Asian, 1.8% were American Indian or Alaska Native; and 14% were Hispanic or Latino. Most patients (63%) had a progressing PN at study entry, 11% had prior treatment with a MEK inhibitor and 36% had prior surgery. Morbidities reported in >25% of patients were pain (70%), disfigurement or major deformity (50%), and motor dysfunction (27%).

Efficacy results are provided in Table 7. The median time to onset of response was 7.8 months (range: 4 months to 19 months) for the adult cohort and 7.9 months (range: 4.1 months to 18.8 months) for the pediatric cohort.

Table 7: Efficacy Results by BICR from ReNeu
 | GOMEKLI Adult (N=58) | GOMEKLI Pediatric (N=56)
Confirmed Overall Response Rate a,b,c,n (%) | 24 (41%) | 29 (52%)
95% CId | (29, 55) | (38, 65)
Duration of Response (DoR)
DoR ≥12 monthse | 21 (88%) | 26 (90%)
DoR ≥24 monthse | 12 (50%) | 14 (48%)

Abbreviations: CI: confidence interval.

a Confirmed overall response was defined as two consecutive assessments of PR or CR assessed within 2- 6 months during the Treatment Phase.

b Patients who had no post-baseline MRI assessment or no confirmed overall response were treated as non-responders.

c All partial responses.

d Obtained using the Clopper-Pearson approach.

e Duration of response was assessed based on observed time.

16 HOW SUPPLIED/STORAGE AND HANDLING

How supplied

GOMEKLI Capsules are supplied as follows:

Capsule Strength | Capsule Description | Package Configuration | NDC
1 mg | Light green body and cap with “MIR 1 mg” printed on the cap in white ink. | Bottle of 42 capsules | 82448-130-42
2 mg | White body and a blue green cap with “MIR 2 mg” printed on the cap in white ink. | Bottle of 42 capsules | 82448-260-42
 |  | Bottle of 84 capsules | 82448-260-84

GOMEKLI Tablets for Oral Suspension are supplied as follows:

Tablet Strength | Tablet Description | Package Configuration | NDC
1 mg | White to off-white, oval, grape flavored tablet, debossed with “S” on one side. | Bottle of 42 tablets | 82448-134-42
 |  | Bottle of 84 tablets | 82448-134-84

Storage and Handling

Store capsules and tablets for oral suspension at 20°C to 25°C (68°F to 77°F). Excursions permitted between 15°C to 30°C (59°F to 86°F). See USP Controlled Room Temperature. Protect from light.

17 PATIENT COUNSELING INFORMATION

Advise the patient or caregiver to read the FDA-approved patient labeling (Patient Information and Instructions for Use).

Ocular Toxicity

Advise patients and caregivers that GOMEKLI can cause serious ocular effects and to immediately contact their healthcare provider if they experience any changes in their vision [see Warnings and Precautions (5.1)].

Left Ventricular Dysfunction

Advise patients and caregivers that GOMEKLI can cause decreased LVEF and to immediately report any signs or symptoms of left ventricular dysfunction to their healthcare provider [see Warnings and Precautions (5.2)].

Dermatologic Adverse Reactions

Advise patients and caregivers that GOMEKLI can cause severe dermatologic adverse reactions and to contact their healthcare provider if they experience any skin reactions [see Warnings and Precautions (5.3)]. Advise patients and caregivers that GOMEKLI can cause alopecia.

Embryo-Fetal Toxicity

Advise pregnant women and females of reproductive potential of the potential risk to a fetus. Advise females of reproductive potential to inform their healthcare provider of a known or suspected pregnancy [see Warnings and Precautions (5.4) and Use in Specific Populations (8.1)].

Contraception

Females

Advise females of reproductive potential to use effective contraception during treatment with GOMEKLI and for 6 weeks after the last dose [see Warnings and Precautions (5.4) and Use in Specific Populations (8.3)].

Males

Advise males with female partners of reproductive potential to use effective contraception during treatment with GOMEKLI and for 3 months after the last dose [see Warnings and Precautions (5.4) and Use in Specific Populations (8.3)].

Lactation

Advise women not to breastfeed during treatment with GOMEKLI and for 1 week after the last dose [see Use in Specific Populations (8.2)].

Infertility

Advise females of reproductive potential that GOMEKLI may impair fertility [see Nonclinical Toxicology (13.1)].

Administration

Advise patients to swallow GOMEKLI capsules whole (do not open, break or chew capsules) [see Dosage and Administration (2.2)].

Advise patients to either swallow GOMEKLI tablets whole or to disperse GOMEKLI tablets in water and administer orally as a liquid [see Dosage and Administration (2.2) and Instructions for Use].

Manufactured for:
SpringWorks Therapeutics, Inc. Stamford, CT 06902
GOMEKLITM is a trademark of SpringWorks Therapeutics, Inc.
©2025 SpringWorks Therapeutics, Inc.

PATIENT INFORMATION

GOMEKLI™ (go-MEK-lee)
(mirdametinib)
capsules

PATIENT INFORMATION

GOMEKLI™ (go-MEK-lee)
(mirdametinib)
tablets for oral suspension

What is GOMEKLI?
GOMEKLI is a prescription medicine used to treat adults and children 2 years of age and older with neurofibromatosis type 1 (NF1) who have plexiform neurofibromas that cause symptoms and cannot be completely removed by surgery.
It is not known if GOMEKLI is safe and effective in children under 2 years of age.

Before taking GOMEKLI tell your healthcare provider about all of your medical conditions, including if you:

- have eye problems
- have heart problems
- are pregnant or plan to become pregnant. GOMEKLI can harm your unborn baby.
  Females who are able to become pregnant:
  - Your healthcare provider should check to see if you are pregnant before you begin treatment with GOMEKLI.
  - Use effective birth control (contraception) during treatment with GOMEKLI and for 6 weeks after your last dose.
  - Tell your healthcare provider right away if you become pregnant or think you may be pregnant during treatment with GOMEKLI.
    Males with female partners who are able to become pregnant:
  - Use effective birth control (contraception) during treatment with GOMEKLI and for 3 months after your last dose.
  - Tell your healthcare provider right away if your female partner becomes pregnant or thinks she may be pregnant during treatment with GOMEKLI.
- are breastfeeding or plan to breastfeed. It is not known if GOMEKLI passes into your breastmilk.
  - Do not breastfeed during treatment with GOMEKLI and for 1 week after your last dose.
  - Talk to your healthcare provider about the best way to feed your baby during this time.

Tell your healthcare provider about all the medicines you take, including prescription and over-the-counter medicines, vitamins, and herbal supplements.

How should I take GOMEKLI?

- Take GOMEKLI exactly as your healthcare provider tells you to take it. Your healthcare provider may change your dose, temporarily stop, or permanently stop treatment with GOMEKLI if you develop certain side effects.
- Take GOMEKLI twice a day, about 12 hours apart, for 21 days, followed by 7 days off treatment, to complete a 28- day treatment cycle. Your healthcare provider will decide how many treatment cycles are right for you.
- Take GOMEKLI with or without food.
- GOMEKLI comes in 2 different dosage forms, GOMEKLI capsules and GOMEKLI tablets for oral suspension. Your healthcare provider will decide the dosage form and dose of GOMEKLI that is right for you.
- If you take GOMEKLI capsules:
  - Swallow each capsule whole with drinking water. If more than 1 capsule is required, swallow 1 capsule at a time.
  - Do not open, break, or chew the capsules
- If you take GOMEKLI tablets for oral suspension, either:
  - Swallow each tablet for oral suspension whole with drinking water. If more than 1 tablet is required, swallow 1 tablet at a time.
    OR
  - Disperse the tablets for oral suspension in drinking water to make a liquid (suspension) before you take or give GOMEKLI.
    See the “Instructions for Use” that come with your medicine for instructions on how to prepare and take GOMEKLI tablets for oral suspension.
- If you miss a dose of GOMEKLI, skip the missed dose and take your next dose at your regularly scheduled time.
- If you vomit at any time after taking GOMEKLI, do not take an additional dose. Take your next dose at your regularly scheduled time.

What are the possible side effects of GOMEKLI?
GOMEKLI may cause serious side effects, including:

- eye problems. GOMEKLI may cause eye problems that can lead to blindness. Your healthcare provider will check your vision before and during treatment with GOMEKLI. Tell your healthcare provider right away if you get any of the following signs or symptoms of eye problems:

- blurred vision

- loss of vision

- other changes to your vision

- heart problems. GOMEKLI may lower the amount of blood pumped by your heart, which is common in children during treatment with GOMEKLI and can also be severe. Your healthcare provider will do tests before you start GOMEKLI treatment, every 3 months during your first year of treatment, and then as needed to make sure your heart is working properly. Tell your healthcare provider right away if you get any of the following signs or symptoms of heart problems:

- coughing or wheezing

- tiredness

- shortness of breath

- increased heart rate

- swelling of your ankles and feet

- skin problems. Skin rashes are common with GOMEKLI in both adults and children and can also be severe. GOMEKLI can also cause hair loss (alopecia). Tell your healthcare provider if you develop any of the following signs or symptoms of skin problems:

- flat skin rash

- skin redness

- raised bumps on the skin

- itchy rash

- skin bumps that look like acne

- peeling skin

The most common side effects of GOMEKLI in adults include:

- diarrhea

- vomiting

- nausea

- tiredness

- muscle, joint, and bone pain

The most common severe abnormal blood tests in adults include an increased enzyme called creatine phosphokinase (CPK).

The most common side effects of GOMEKLI in children include:

- diarrhea

- headache

- muscle, joint, and bone pain

- skin redness, swelling, or pain around the fingernails or toenails

- stomach (abdominal) pain

- nausea

- vomiting

The most common severe abnormal blood tests in children include decreased white blood cell (neutrophil) counts and increased CPK.
GOMEKLI may cause fertility problems in females, which may affect your ability to have children. Talk to your healthcare provider if you have concerns about fertility.
These are not all of the possible side effects of GOMEKLI.
Call your doctor for medical advice about side effects. You may report side effects to FDA at 1-800-FDA-1088.

How should I store GOMEKLI?

- Store GOMEKLI at room temperature between 68°F to 77°F (20°C to 25°C).
- Protect from light.

Keep GOMEKLI and all medicines out of the reach of children.

General information about the safe and effective use of GOMEKLI.
Medicines are sometimes prescribed for purposes other than those listed in a Patient Information leaflet. Do not use GOMEKLI for a condition for which it is not prescribed. Do not give GOMEKLI to other people even if they have the
same symptoms you have. It may harm them. You can ask your pharmacist or healthcare provider for information about GOMEKLI that is written for health professionals.

What are the ingredients in GOMEKLI?
Active ingredient: mirdametinib
Inactive ingredients:
capsule contains: croscarmellose sodium, magnesium stearate and microcrystalline cellulose. The capsule shell contains: FD&C blue #1, gelatin, titanium dioxide, and yellow iron oxide. The printing ink contains: butyl alcohol, dehydrated alcohol, isopropyl alcohol, potassium hydroxide, propylene glycol, purified water, shellac, strong ammonia solution, and titanium dioxide.
tablet for oral suspension contains: croscarmellose sodium, magnesium stearate, microcrystalline cellulose, grape flavor, and sucralose. The grape flavor includes corn syrup solids, modified corn starch, and triacetin.
Manufactured for SpringWorks Therapeutics, Inc. Stamford, CT 06902
GOMEKLITM is a trademark of SpringWorks Therapeutics, Inc.
©2025 SpringWorks Therapeutics, Inc.
For more information call 1-888-400-7989 or visit www.GOMEKLI.com

This Patient Information has been approved by the U.S. Food and Drug Administration Issued: 02/2025

INSTRUCTIONS FOR USE
GOMEKLI™ (go-MEK-lee)
(mirdametinib)
tablets for oral suspension

GOMEKLI tablets for oral suspension can be swallowed whole or prepared and taken as a liquid (oral suspension).

This Instructions for Use contains information on how to prepare and take GOMEKLI tablets for oral suspension as an oral suspension.

Important Information You Need to Know Before Taking GOMEKLI Tablets for Oral Suspension

- Read these Instructions for Use before you or your child start taking GOMEKLI tablets for oral suspension for the first time and each time you get a refill. There may be new information.
- This information does not take the place of talking to your healthcare provider about your or your child’s medical condition or treatment.
- GOMEKLI tablets for oral suspension is for oral use only (taken by mouth).
- Take GOMEKLI tablets for oral suspension with or without food.
- Your healthcare provider will tell you how many GOMEKLI tablets for oral suspension you will need for your or your child’s dose. Always take GOMEKLI tablets for oral suspension exactly as your healthcare provider tells you.
- If you have any questions about how to prepare and take or give a dose of GOMEKLI tablets for oral suspension, talk to your healthcare provider or pharmacist.

Supplies you will need to take or give GOMEKLI tablets for oral suspension
To prepare and take or give GOMEKLI tablets for oral suspension, you will need:

- the prescribed number of GOMEKLI tablets for oral suspension
- a dosing cup provided by your healthcare provider or pharmacist
- if necessary, a 10 mL oral syringe provided by your healthcare provider or pharmacist
- about 10 mL to 20 mL of drinking water

Preparing GOMEKLI tablets for oral suspension

Step 1: Wash and dry your hands before preparing GOMEKLI tablets for oral suspension.

Step 2: Add about 5 mL to 10 mL of drinking water to the dosing cup. Note: The amount of water does not need to be exact.
Only use water to prepare the dose.

Step 3: Count the prescribed number of tablets into your hand.

Step 4: Add the prescribed number of tablets to the water.

Step 5: Swirl the dosing cup gently to disperse the tablets until no lumps remain.
It will take about 2 to 4 minutes to fully disperse the tablets in the water.
GOMEKLI oral suspension will be white and cloudy and there will be some medicine (residue) visible. Try not to spill any of the prepared oral suspension. If you spill the oral suspension, see “Section C. Cleaning up spilled GOMEKLI oral suspension.“
Important: Take or give GOMEKLI oral suspension right away after preparing the dose. If you cannot take or give it right way, take or give GOMEKLI oral suspension within 30 minutes of preparing the dose.

Section A. Taking or giving GOMEKLI oral suspension by swallowing the oral suspension directly from the dosing cup.
Note: To use an oral syringe to take or give GOMEKLI oral suspension, skip to Section B.

Step A1: Take or give the GOMEKLI oral suspension from the dosing cup right away after preparing the dose.
If more than 30 minutes have passed since you prepared the dose, throw away (dispose of) the GOMEKLI oral suspension and start over from Step 1. See “Section D. Disposing of GOMEKLI tablets for oral suspension.”
If you are not sure how to throw away the GOMEKLI oral suspension, ask your healthcare provider or pharmacist.
Important: After swallowing the oral suspension, there will be some medicine (residue) still inside the dosing cup. The residue may be hard to see. Follow Steps A2 through A4 to make sure that the full dose of GOMEKLI is taken or given.

Step A2: Add another 5 mL to 10 mL of drinking water to the same dosing cup.

Step A3: Swirl the dosing cup gently.

Step A4: Drink or give the water and residue mixture from the dosing cup.

Step A5: Wash the dosing cup with clean water. Allow the dosing cup to dry completely before storing.
Wash your hands when you are finished.

Section B. Taking or giving GOMEKLI oral suspension from an oral syringe.

Step B1: Place the tip (open end) of the oral syringe into the prepared medicine and draw up all the GOMEKLI oral suspension from the dosing cup into the oral syringe by pulling back on the plunger.
Important: Take or give the GOMEKLI oral suspension from the oral syringe right away after preparing the dose.
If more than 30 minutes have passed since you prepared the dose, throw away the GOMEKLI oral suspension and start over from Step
1. See “Section D. Disposing of GOMEKLI oral suspension or GOMEKLI tablets for oral suspension.”
If you are not sure how to throw away the GOMEKLI oral suspension, ask your healthcare provider or pharmacist.

Step B2: Place the tip of the oral syringe inside the mouth pointing toward the inside of either cheek.
If you are giving a dose of GOMEKLI oral suspension to a child, make sure they are sitting upright until all the liquid has been swallowed.

Step B3: Slowly push the plunger all the way down to give the full dose of GOMEKLI. Allow time for all the medicine to be swallowed.
Important: After swallowing the oral suspension, there will be some medicine (residue) still inside the dosing cup and oral syringe. The residue may be hard to see. Follow Steps B4 through B6 to make sure that the full dose of GOMEKLI is given.

Step B4: Add another 5 to 10 mL of drinking water to the same dosing cup.

Step B5: Swirl the dosing cup gently.

Step B6: Place the tip of the oral syringe into the dosing cup and draw the water and residue mixture into the oral syringe by pulling back on the plunger. Take or give all of the water and residue mixture to the child. Allow time for the water and residue mixture to be swallowed.

Step B7: Wash the dosing cup and oral syringe with clean water. Pull the plunger out of the oral syringe and wash the oral syringe parts separately.
Allow the parts to dry completely before reassembling and storing.
Wash your hands when you are finished.

Section C. Cleaning up spilled GOMEKLI oral suspension

- If you accidentally spill any GOMEKLI oral suspension, soak up the spilled GOMEKLI oral suspension completely using an absorbent material, such as paper towels, and throw away (dispose of) in the trash.
- Wash your hands with soap and water.

Section D. Disposing of GOMEKLI oral suspension or GOMEKLI tablets for oral suspension

- If it has been more than 30 minutes since you prepared your dose of GOMEKLI oral suspension or if you have any unused prepared oral suspension, throw away the prepared oral suspension in the trash.
- Throw away unused or expired GOMEKLI tablets for oral suspension in the trash.

Section E. Storing GOMEKLI tablets for oral suspension

- Store GOMEKLI tablets for oral suspension at room temperature between 68°F to 77°F (20°C to 25°C).
- Protect from light.

Keep GOMEKLI tablets for oral suspension and all medicines out of the reach of children.

Manufactured for SpringWorks Therapeutics, Inc. Stamford, CT 06902
GOMEKLITM is a trademark of SpringWorks Therapeutics, Inc.
©2025 SpringWorks Therapeutics, Inc.
For more information call 1-888-400-7989 or visit www.GOMEKLI.com

This Instructions for Use has been approved by the U.S. Food and Drug Administration. Issued: 02/2025

PRINCIPAL DISPLAY PANEL

NDC 82448-134-84
GOMEKLITM
(mirdametinib)
Tablets for oral suspension
1 mg
per tablet
84 Tablets

PRINCIPAL DISPLAY PANEL

NDC 82448-134-42
GOMEKLITM
(mirdametinib)
Tablets for oral suspension
1 mg
per tablet
42 Tablets

PRINCIPAL DISPLAY PANEL

NDC 82448-130-42
GOMEKLITM
(mirdametinib)
Capsules
1 mg
per Capsules
42 Capsules

PRINCIPAL DISPLAY PANEL

NDC 82448-260-42
GOMEKLITM
(mirdametinib)
Capsules
2 mg
per Capsules
42 Capsules

PRINCIPAL DISPLAY PANEL

NDC 82448-260-84
GOMEKLITM
(mirdametinib)
Capsules
2 mg
per Capsules
84 Capsules